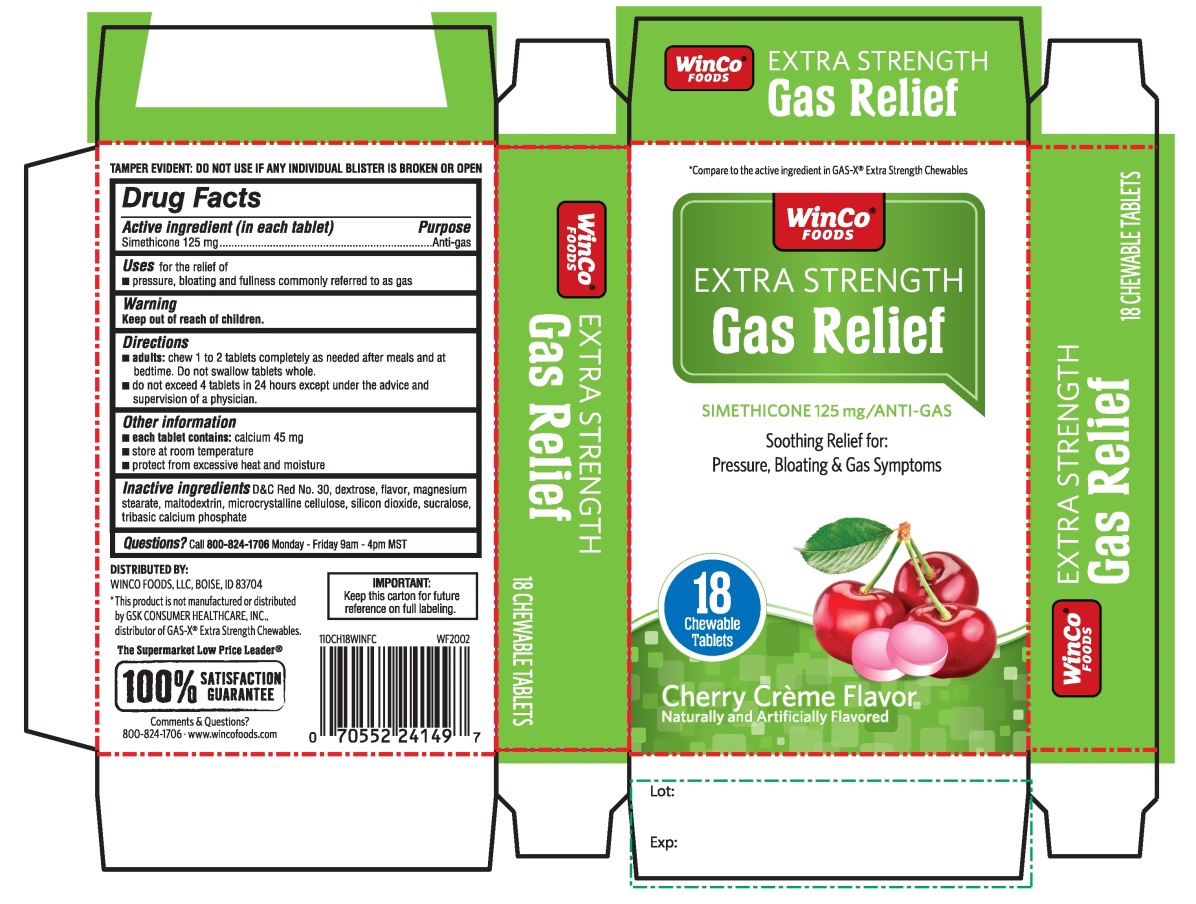 DRUG LABEL: WinCo FOODS Extra Strength

NDC: 67091-361 | Form: TABLET, CHEWABLE
Manufacturer: WINCO FOODS, LLC
Category: otc | Type: HUMAN OTC DRUG LABEL
Date: 20251202

ACTIVE INGREDIENTS: DIMETHICONE, UNSPECIFIED 125 mg/1 1
INACTIVE INGREDIENTS: D&C RED NO. 30; DEXTROSE, UNSPECIFIED FORM; MAGNESIUM STEARATE; MALTODEXTRIN; MICROCRYSTALLINE CELLULOSE; SILICON DIOXIDE; SUCRALOSE; TRIBASIC CALCIUM PHOSPHATE

WinCo®FOODS Extra Strength Gas Relief Simethicone

Active ingredient (in each tablet)

Simethicone 125 mg

Purpose

Anti-gas

Uses

for the relief of

- pressure, bloating and fullness commonly referred to as gas

Directions

- adults: chew 1 to 2 tablets as needed after meals and at bedtime. Do not swallow tablets whole.
- do not exceed 4 tablets in a 24 hours except under the advice and supervision of a physician.

Other information

- each tablets contains:calcium 45 mg
- store at room temperature
- protect from excessive heat and moisture

TAMPER EVIDENT: DO NOT USE IF ANY INDVIDUAL BLISTER IS BROKEN OR OPEN

Inactive ingredients

D&C Red No. 30, dextrose, flavor, magnesium stearate, maltodextrin, microcrystalline cellulose, silicon dioxide, sucralose, tribasic calcium phosphate.

Principal Display Panel

WinCo®FOODS

NDC 67091-361-18

*Compare to the active ingredient in GAS-X®Extra Strength Chewables

EXTRA STRENGTH

Gas Relief

SIMETHICONE 125 mg/ANTI-GAS

Soothing Relieves for:

Pressure, Bloating & Gas Distress

Cherry Creme Flavor

Naturally And Artificially Flavored

18 Chewable Tablets

DISTRIBUTED BY:

WINCO FOODS, LLC, BOISE, ID 83704

*This product is not manufactured or distributed by GSK CONSUMER HEALTHCARE, INC. distributor of Gas-X®Extra strength Chewables

The Supermarket Low Price Leader®

100% SATISFACTION GUARANTEED

Comments & Questions?

800-824-1706 www.wincofoods.com

IMPORTANT:Keep this carton for future reference on full labeling.